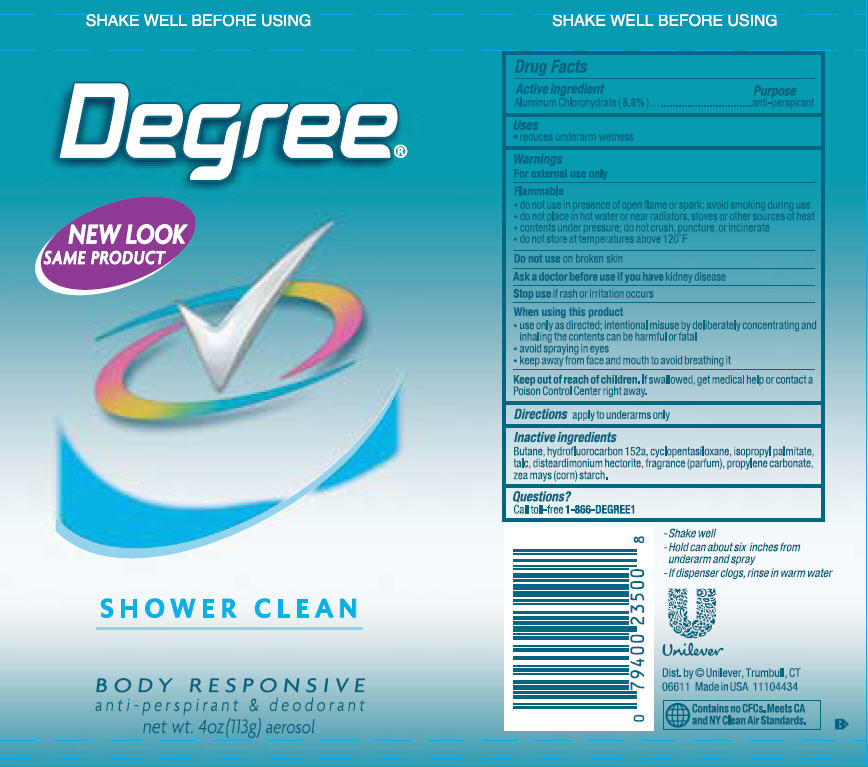 DRUG LABEL: Degree
NDC: 64942-1151 | Form: AEROSOL, SPRAY
Manufacturer: Conopco Inc. d/b/a Unilever
Category: otc | Type: HUMAN OTC DRUG LABEL
Date: 20101216

ACTIVE INGREDIENTS: Aluminum Chlorohydrate 8.8 g/100 g
INACTIVE INGREDIENTS: BUTANE; CYCLOMETHICONE 5; ISOPROPYL PALMITATE; TALC; PROPYLENE CARBONATE; STARCH, CORN; DISTEARYLDIMONIUM CHLORIDE; HECTORITE

Degree Shower Clean Aerosol Antiperspirant Deodorant

Active ingredient

Aluminum chlorohydrate (8.8%)

Purpose
anti-perspirant

Uses
· reduces underarm wetness

WARNINGS
For external use only
FLAMMABLE
do not use in presence of open flame or spark; avoid smoking during use
do not place in hot water or near radiators, stoves or other sources of heat
contents under pressure; so not crush, puncture or incinerate
do not store at temperatures above 120 degrees F
Do not use on broken skin
Ask a doctor before use if you have kidney disease
Stop use if rash or irritation occurs
When using this product
use only as directed; intentional misuse by deliberately concentrating and inhaling the contents can be harmful or fatal
avoid spraying in eyes
keep away from face and mouth to avoid breathing it

Keep out of reach of children. If swallowed, get medical help or contact a Poison Control Center right away.

Directions
apply to underarms only

Inactive ingredients
Butane
hydrofluorcarbon 152a
cyclopentasiloxane
isopropyl palmitate
talc
disteardimonium hectorite
fragrance(parfum)
propylene carbonate
zea mays (corn) starch

Questions?
call toll-free 1-866-DEGREE1

PACKAGE LABEL

6 oz PDP